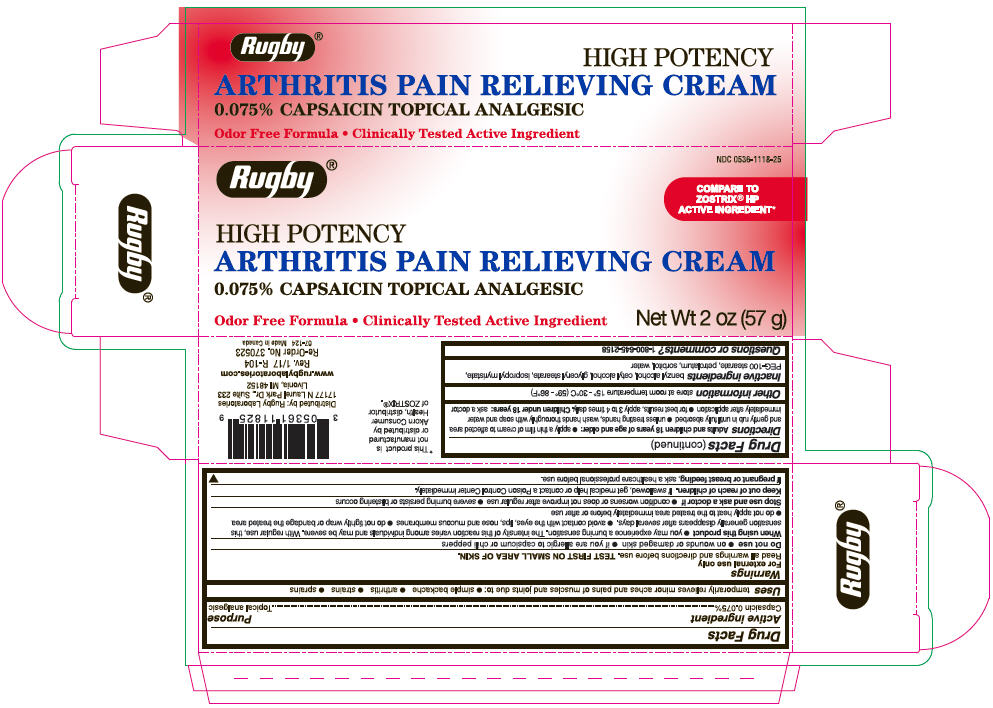 DRUG LABEL: Rugby Arthritis Pain Relieving
NDC: 0536-1118 | Form: CREAM
Manufacturer: Rugby Laboratories
Category: otc | Type: HUMAN OTC DRUG LABEL
Date: 20240314

ACTIVE INGREDIENTS: Capsaicin 0.75 mg/1 g
INACTIVE INGREDIENTS: Benzyl Alcohol; Cetyl Alcohol; GLYCERYL MONOSTEARATE; Isopropyl Myristate; PEG-100 Stearate; Petrolatum; Sorbitol; Water

Rugby ® Arthritis Pain Relieving Cream

Drug Facts

Active ingredient

Capsaicin 0.075%

Purpose

Topical Analgesic

Uses

temporarily relieves minor aches and pains of muscles and joints due to:

- simple backache
- arthritis
- strains
- sprains

Warnings

For external use only

Read all warnings and directions before use. TEST FIRST ON SMALL AREA OF SKIN.

Do not use

- on wounds or damaged skin
- if you are allergic to capsicum or chili peppers

When using this product

- you may experience a burning sensation. The intensity of this reaction varies among individuals and may be severe. With regular use, this sensation generally disappears after several days.
- avoid contact with eyes, lips, nose and mucous membranes
- do not tightly wrap or bandage the treated area
- do not apply heat to the treated area immediately before or after use

Stop and ask a doctor if

- condition worsens or does not improve after regular use
- severe burning persists or blistering occurs

Keep out of reach of children. If swallowed, get medical help or contact a Poison Control Center immediately.

PREGNANCY OR BREAST FEEDING

If pregnant or breast feeding, ask a health professional before use.

Directions

Adults and children 18 years of age and older:

- apply a thin film of cream to affected area and gently rub in until fully absorbed
- unless treating hands, wash hands thoroughly with soap and water immediately after application
- for best results, apply 3 to 4 times daily.

Children under 18 years: ask a doctor

Other information

Store at room temperature 15° - 30°C (59°F – 86°F).

Inactive ingredients

benzyl alcohol, cetyl alcohol, glyceryl stearate, isopropyl myristate, PEG-100 stearate, petrolatum, sorbitol, water

Questions or comments?

1-800-645-2158

Distributed by: Rugby Laboratories
17177 N Laurel Park Dr., Suite 233
Livonia, MI 48152

PRINCIPAL DISPLAY PANEL - 57 g Tube Carton

NDC 0536-1118-25

Rugby ®

COMPARE TO
ZOSTRIX® HP
ACTIVE INGREDIENT*

HIGH POTENCY
ARTHRITIS PAIN RELIEVING CREAM
0.075% CAPSAICIN TOPICAL ANALGESIC

Odor Free Formula • Clinically Tested Active Ingredient
Net Wt 2 oz (57 g)